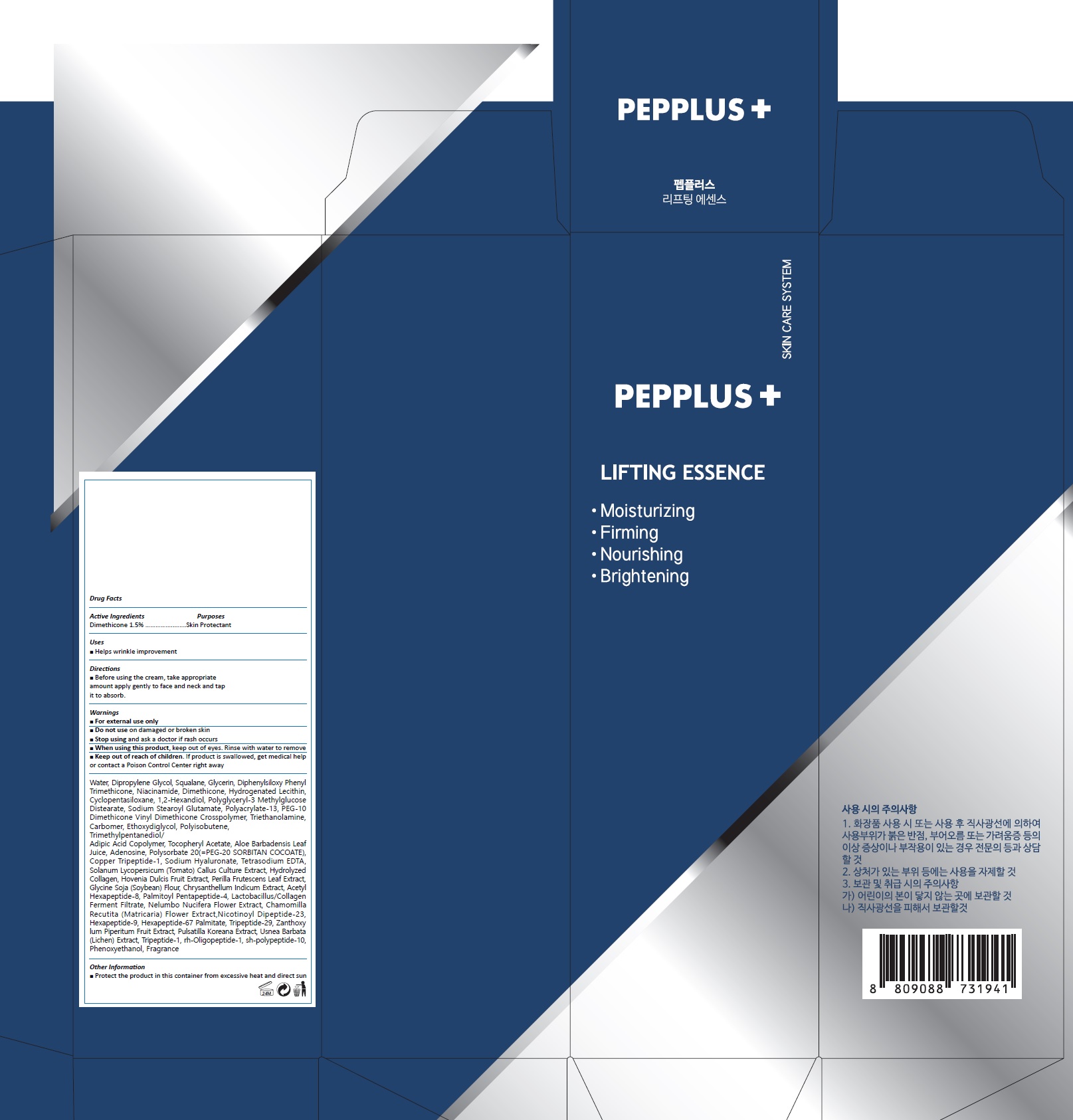 DRUG LABEL: PEPPLUS LIFTING ESSENCE
NDC: 72211-010 | Form: CREAM
Manufacturer: Picobio Co., Ltd
Category: otc | Type: HUMAN OTC DRUG LABEL
Date: 20211102

ACTIVE INGREDIENTS: DIMETHICONE 1.5 g/100 mL
INACTIVE INGREDIENTS: WATER; DIPROPYLENE GLYCOL; SQUALANE; GLYCERIN; PHENYL TRIMETHICONE; NIACINAMIDE; HYDROGENATED SOYBEAN LECITHIN; CYCLOMETHICONE 5

72211-010_PEPPLUS LIFTING ESSENCE

ACTIVE INGREDIENT

DIMETHICONE 1.50%

PURPOSE

Skin Protectant

INDICATIONS AND USAGE

Helps wrinkle improvement

DOSAGE AND ADMINISTRATION

Before using the cream, take appropriate
amount apply gently to face and neck and tap
it to absorb.

WARNINGS

For external use only.
Do not use on damaged or broken skin.
When using this product, keep out of eyes. Rinse with water to remove.
Stop using and ask a doctor if rash occurs.

KEEP OUT OF REACH OF CHILDREN

Keep out of reach of the children. If product is swallowed, get medical help or contact a poison control center right away.

INACTIVE INGREDIENT

Water, Dipropylene Glycol, Squalane, Glycerin, Phenyl Trimethicone, Niacinamide, Hydrogenated Lecithin, Cyclopentasiloxane, Perilla Frutescens Leaf Extract, Nelumbo Nucifera Flower Extract, Lactobacillus/Collage, Ferment Filtrate, Hydrolyzed Collagen, Sodium Hyaluronate, Chamomilla Recutita (Matricaris) Flower Extract, Glycine Soja (Soybean) Flour, Chrysanthellum Indicum Extract, Hovenia Dulcis Fruit Extract, Solanum Lycopersicum (Tomato) Fruit/Leaf/Stem Extract, Aloe Barbadensis Leaf Juice, Polyglyceryl-3 Methylglucose Distearate, PEG-10 Dimethicone/Vinyl Dimethicone Crosspolymer, Phenoxyethanol, Sodium Stearoyl Glutamate, Ethoxydiglycol, Polysorbate 20, Trimethylpentanediol/Adipic Acid Copolymer, 1,2-Hexanediol, Carbomer, Triethanolamine, Polyisobutene, Adenosine, Polyacrylate-13, Tetrasodium EDTA, Tocopheryl Acetate, Copper Tripeptide-1, Acety, Hexapeptide-8, Palmitoyl Pentapeptide-4, Nicotinoyl Dipeptide-23, Hexapeptide-67 Palmitate, Tripeptide-1, Tripeptide-29, Hexapeptide-9, sh-polypeptide-10, sh-polypeptide-1, rh-Oligopeptide-1, Perfume